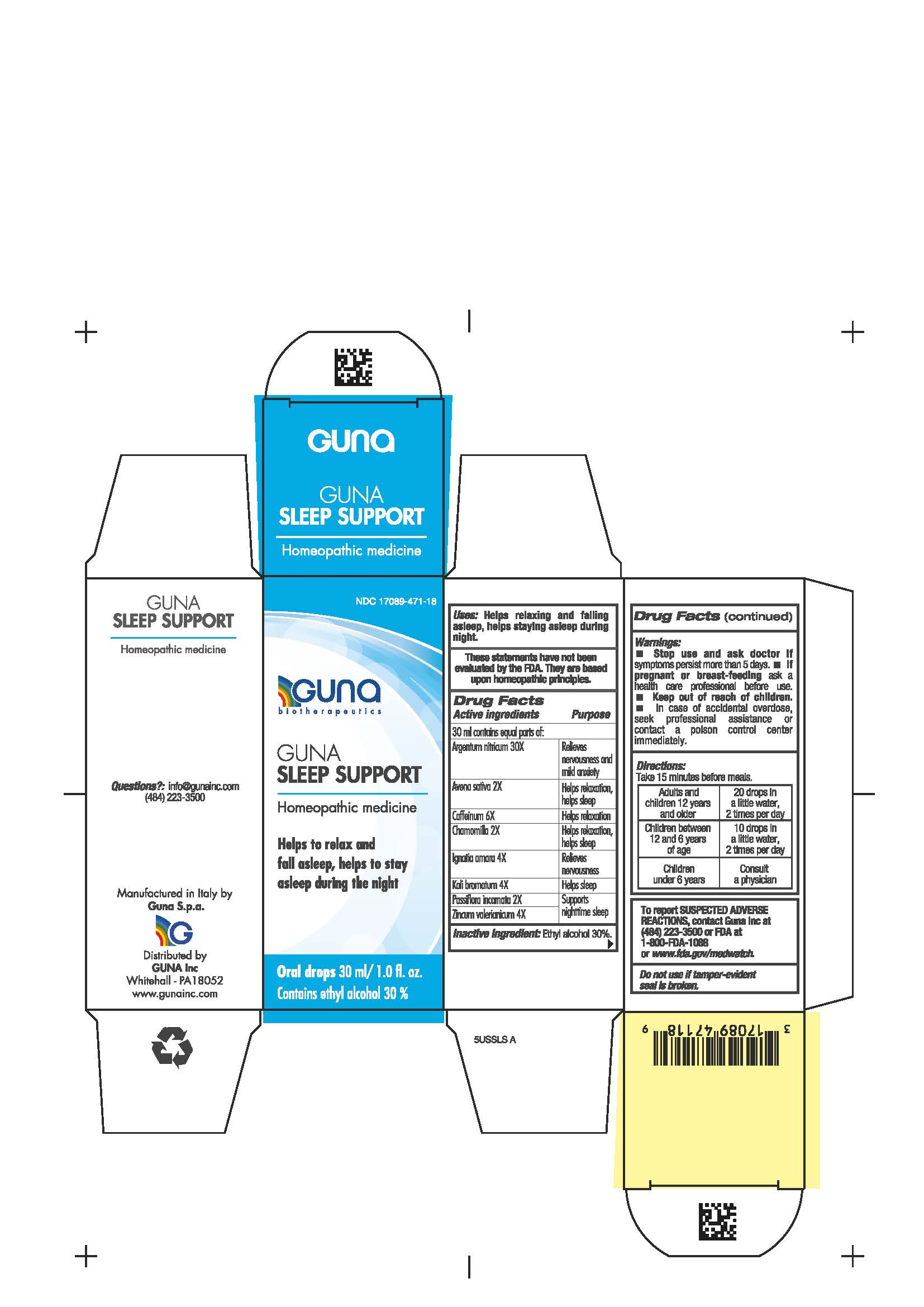 DRUG LABEL: GUNA SLEEP SUPPORT
NDC: 17089-471 | Form: SOLUTION/ DROPS
Manufacturer: Guna spa
Category: homeopathic | Type: HUMAN OTC DRUG LABEL
Date: 20210117

ACTIVE INGREDIENTS: POTASSIUM BROMIDE 4 [hp_X]/30 mL; CAFFEINE 6 [hp_X]/30 mL; AVENA SATIVA FLOWERING TOP 2 [hp_X]/30 mL; MATRICARIA CHAMOMILLA WHOLE 2 [hp_X]/30 mL; STRYCHNOS IGNATII SEED 4 [hp_X]/30 mL; PASSIFLORA INCARNATA FLOWERING TOP 2 [hp_X]/30 mL; SILVER NITRATE 30 [hp_X]/30 mL; ZINC VALERATE DIHYDRATE 4 [hp_X]/30 mL
INACTIVE INGREDIENTS: ALCOHOL

GUNA SLEEP SUPPORT

Uses:

- Helps to relax and fall asleep,
- Helps to stay asleep during the night

INDICATIONS AND USAGE

Take 15 minutes before meals.

inactive ingredient: Ethyl alcohol 30%.

Questions?: info@gunainc.com
Tel. (484) 223-3500

DOSAGE AND ADMINISTRATION

Adults and children 12 years and older: 20 drops in a little water, 2 times per day
Children between 12 and 6 years of age: 10 drops in a little water, 2 times per day
Children under 6 years: consulta a physician

Keep out of reach of children

PREGNANCY OR BREAST FEEDING

If pregnant or breast-feeding ask a health care professional before use

- Stop use and ask doctor if symptoms persist more than 5 days.
- If pregnant or breast-feeding ask a health care professional before use.
- Keep out of reach of children. In case of overdose, get professional assistance or contact a Poison Control Center immediately.
- Contains ethyl alcohol 30%

active ingredient/purpose

Avena sativa 2X Helps relaxation, helps sleep

Chamomilla 2X Helps relaxation, helps sleep

Caffeinum 6X Helps relaxation

Ignatia amara 4X Relieves nervousness

Kali bromatum 4X Helps sleep

Passiflora incarnata 2X Supports nighttime sleep

Zincum valerianicum 4X Supports nighttime sleep